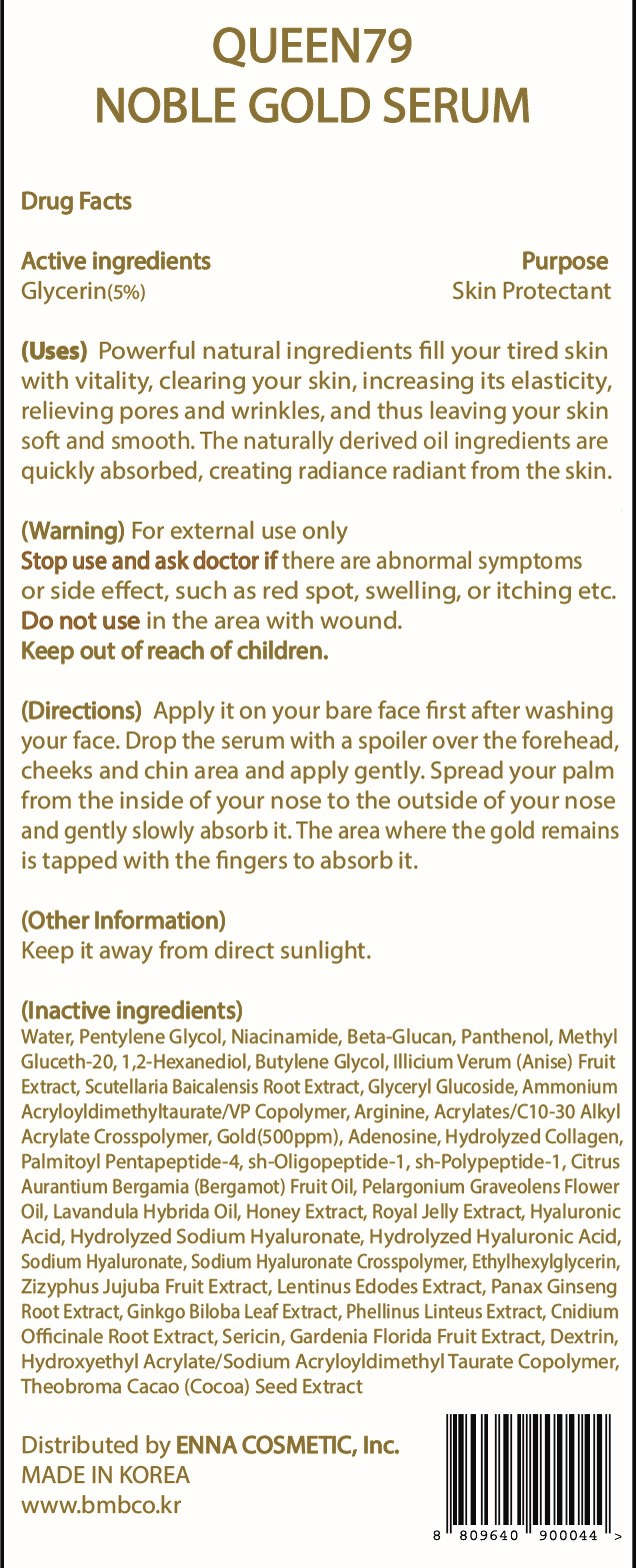 DRUG LABEL: QUEEN79 NOBLE GOLD SERUM
NDC: 81810-302 | Form: CREAM
Manufacturer: ENNA COSMETIC, Inc.
Category: otc | Type: HUMAN OTC DRUG LABEL
Date: 20230531

ACTIVE INGREDIENTS: GLYCERIN 5 mg/100 mL
INACTIVE INGREDIENTS: WATER; ARGININE; BASIC FIBROBLAST GROWTH FACTOR (HUMAN); HONEY; HYALURONATE SODIUM; GINKGO; CNIDIUM OFFICINALE ROOT; ASIAN GINSENG; HYDROXYETHYL ACRYLATE/SODIUM ACRYLOYLDIMETHYL TAURATE COPOLYMER (100000 MPA.S AT 1.5%); ETHYLHEXYLGLYCERIN; PELARGONIUM GRAVEOLENS FLOWER OIL; GARDENIA JASMINOIDES FRUIT; METHYL GLUCETH-20; COCOA; PENTYLENE GLYCOL; NIACINAMIDE; 1,2-HEXANEDIOL; PANTHENOL; BUTYLENE GLYCOL; STAR ANISE FRUIT; SCUTELLARIA BAICALENSIS ROOT; AMMONIUM ACRYLOYLDIMETHYLTAURATE/VP COPOLYMER; GOLD; ADENOSINE; NEPIDERMIN; PALMITOYL PENTAPEPTIDE-4; BERGAMOT OIL; LAVANDIN OIL; HYALURONIC ACID; JUJUBE FRUIT; LENTINULA EDODES MYCELIUM

81810-302 QUEEN79 NOBLE GOLD SERUM

Active ingredients

Glycerin(5%)

Purpose

Skin Protectant

Uses

Powerful natural ingredients fill your tired skin with vitality, clearing your skin, increasing its elasticity, relieving pores and wrinkles, and thus leaving your skin soft and smooth. The naturally derived oil ingredients are quickly absorbed, creating radiance radiant from the skin.

Warning

For external use only

Stop use and ask doctor if

there are abnormal symptoms or side effects, such as red spot, swelling, or itching etc.

Do not use

in the area with wound.

Keep out of reach of children

Directions

Apply it on your bare face first after washing your face, Drop the serum with a spoiler over the forehead, cheeks and chin area apply gently. Spread your palm from the inside of your nose to the outside of your nose and gently slowly absorb it. The area where the gold remains is tapped with the fingers to absorb it.

Other Information

Keep it away from direct sunlight.

Inactive ingredients

WATER, PENTYLENE GLYCOL, NIACINAMIDE, BETA-GLUCAN, PANTHENOL, METHYL GLUCETH-20, 1,2-HEXANEDIOL, BUTYLENE GLYCOL, ILLICIUM VERUM (ANISE) FRUIT EXTRACT, SCUTELLARIA BAICALENSIS ROOT EXTRACT, GLYCERYL GLUCOSIDE, AMMONIUM ACRYLOYLDIMETHYLTAURATE/VP COPOLYMER, ARGININE, ACRYLATES/C10-30 ALKYL ACRYLATE CROSSPOLYMER, GOLD(500ppm), ADENOSINE, ETHYLHEXYLGLYCERIN, HYDROLYZED COLLAGEN, PAMITOYL PENTAPEPTIDE-4, SH-OLIGOPEPTIDE-1, SH-POLYPEPTIDE-1, CITRUS AURANTIUM BERGAMIA (BERGAMOT) FRUIT OIL, PELARGONIUM GRAVEOLENS FLOWER OIL, LAVANDULA HYBRIDA OIL, HONEY EXTRACT, ROYAL JELLY EXTRACT, HYALURONIC ACID, HYDROLYZED SODIUM HYALURONATE, HYDROLYZED HYALURONIC ACID, SODIUM HYALURONATE, SODIUM HYALURONATE CROSSPOLYMER, ETHYLHEXYLGLYCERIN, ZIZYPHUS JUJUBA FRUIT EXTRACT, LENTINUS EDODES EXTRACT, PANAX GINSENG ROOT EXTRACT, GINKGO BILOBA LEAF EXTRACT, PHELLINUS LINTEUS EXTRACT, CNIDIUM OFFICINALE ROOT EXTRACT, SERICIN, GARDENIA FLORIDA FRUIT EXTRACT, DEXTRIN, HYDROXYETHYL ACRYLATE/SODIUM ACRYLOYLDIMETHYL TAURATE COPOLYMER, THEOBROMA CACAO (COCOA) SEED EXTRACT,